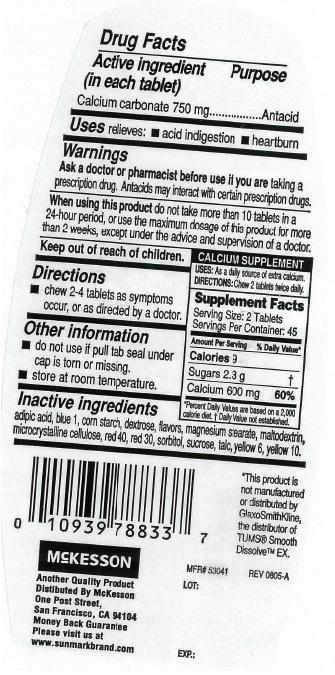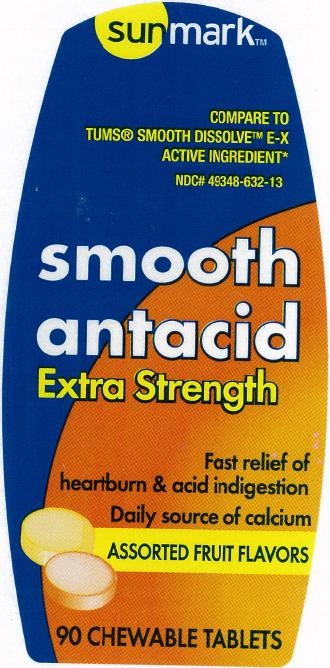 DRUG LABEL: Sunmark smooth antacid 
                
NDC: 49348-632 | Form: TABLET, CHEWABLE
Manufacturer: McKesson
Category: otc | Type: HUMAN OTC DRUG LABEL
Date: 20121016

ACTIVE INGREDIENTS: CALCIUM CARBONATE 750 mg/1 1
INACTIVE INGREDIENTS: ADIPIC ACID; D&C YELLOW NO. 10; D&C RED NO. 30; DEXTROSE; FD&C RED NO. 40; FD&C YELLOW NO. 6; FD&C BLUE NO. 1; MAGNESIUM STEARATE; STARCH, CORN; SORBITOL; SUCROSE; TALC; MALTODEXTRIN; CELLULOSE, MICROCRYSTALLINE

Sunmark Smooth Antacid Extra Strength

Active ingredient (in each tablet)

Calcium carbonate 750 mg

Purpose

Antacid

Uses

relieves:

- acid indigestion
- heartburn

Warnings

Ask a doctor or pharmacist before use if you are

taking a prescription drug. Antacids may interact with certain prescription drugs.

When using this product

do not take more than 10 tablets in a 24-hour period, or use the maximum dosage of this product for more than 2 weeks, except under the advice and supervision of a doctor.

Keep out of reach of children

Directions

chew 2-4 tablets as symptoms occur, or as directed by a doctor

Other information

- do not use if pull tab seal under cap is torn or missing
- store at room temperature

Inactive ingredients

adipic acid, blue 1, corn starch, dextrose, flavors, magnesium stearate, maltodextrin, microcrystalline cellulose, red 40, red 30, sorbitol, sucrose, talc, yellow 6, yellow 10

PDP

sunmark

COMPARE TO TUMS® SMOOTH DISSOLVE E-X ACTIVE INGREDIENT

smooth antacid

Extra Strength

Fast relief of heartburn and acid indigestion

Daily source of calcium

ASSORTED FRUIT FLAVORS
90 CHEWABLE TABLETS